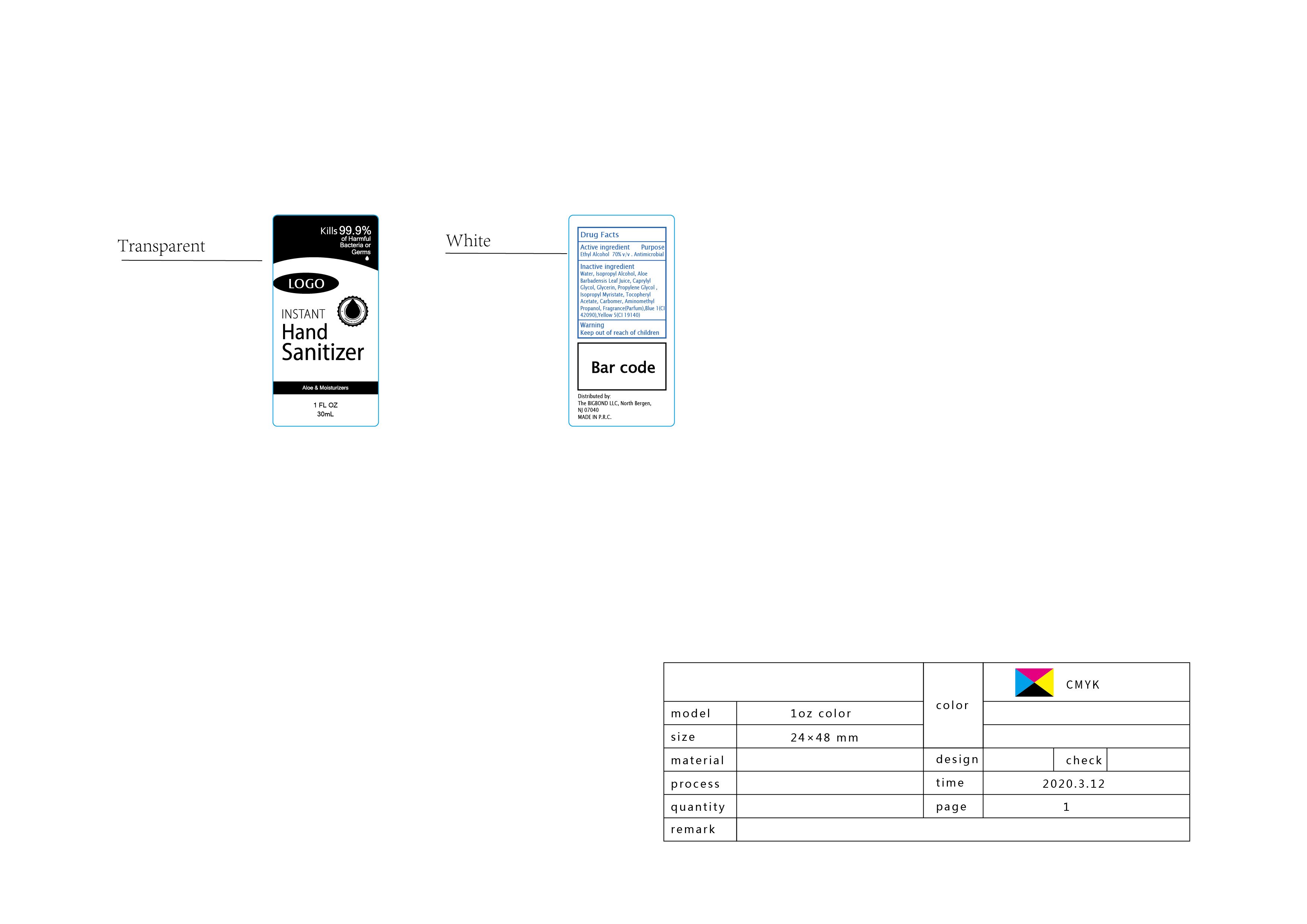 DRUG LABEL: Instant hand sanitizer
NDC: 87052-011 | Form: LIQUID
Manufacturer: THE BIGBOND LLC
Category: otc | Type: HUMAN OTC DRUG LABEL
Date: 20210203

ACTIVE INGREDIENTS: ALCOHOL 21 mL/30 mL
INACTIVE INGREDIENTS: PROPYLENE GLYCOL; ISOPROPYL ALCOHOL; .ALPHA.-TOCOPHEROL ACETATE; CARBOMER HOMOPOLYMER, UNSPECIFIED TYPE; GLYCERIN; ALOE VERA LEAF; CAPRYLYL GLYCOL; AMINOMETHYLPROPANOL; FD&C YELLOW NO. 5; WATER; FD&C BLUE NO. 1

DOSAGE AND ADMINISTRATION

1.5m1-3 5ml/time; Store below 110°F (43°C) ; May discolor certain fabrics of surfaces

WARNINGS

keep out of reach of childen

INACTIVE INGREDIENT

Water, Isopropyl Alcohol, Aloe Barbadensis Leaf Juice, Caprylyl Glycol, Glycerin, Propylene Glycol ,Isopropyl Myristate, Tocopheryl Acetate, Carbomer, Aminomethyl Propanol

INDICATIONS AND USAGE

Take appropriate amount of this product to moisten your hands and rub for one minute until the liquid covers the whole surface

keep out oreeceh of cildlen

PURPOSE

Disinfection
Sterilization
No Rinseing

ACTIVE INGREDIENT

Ethyl alcohol